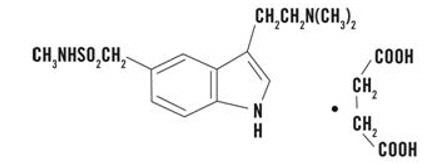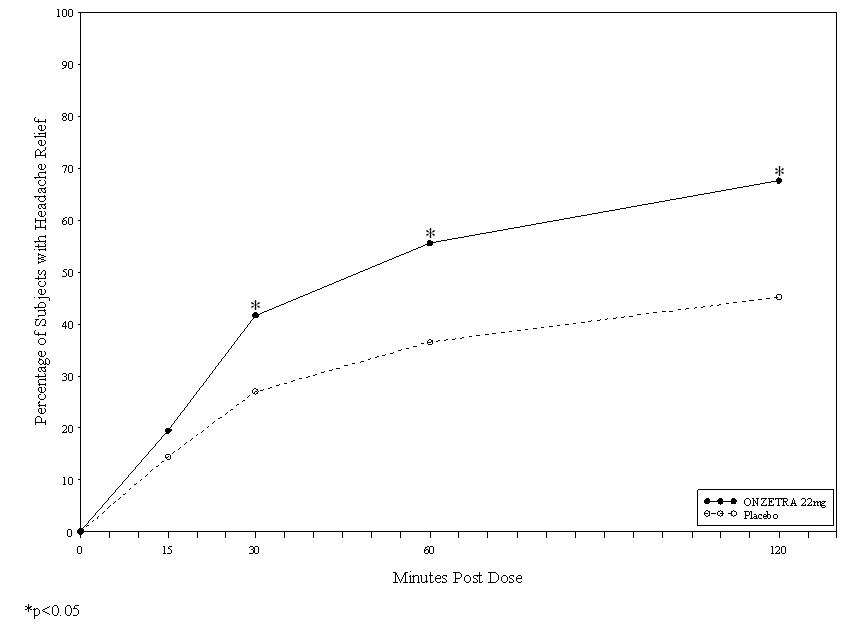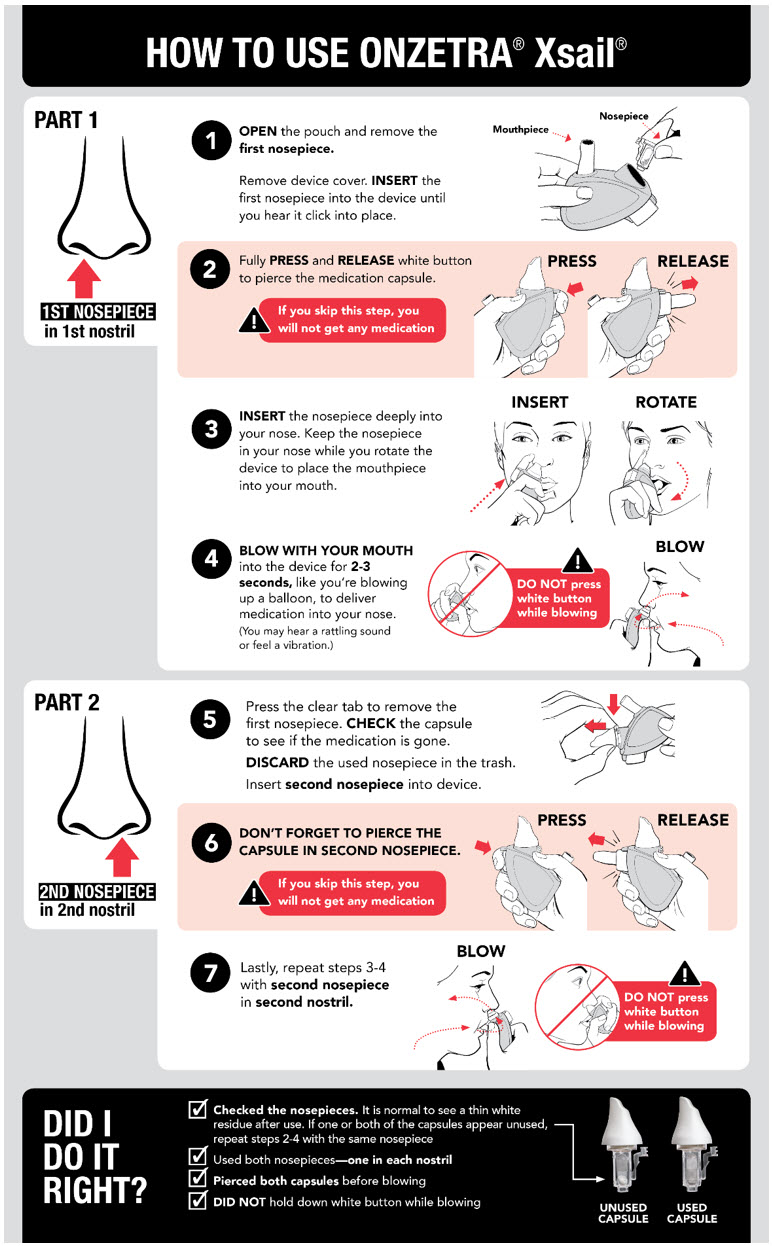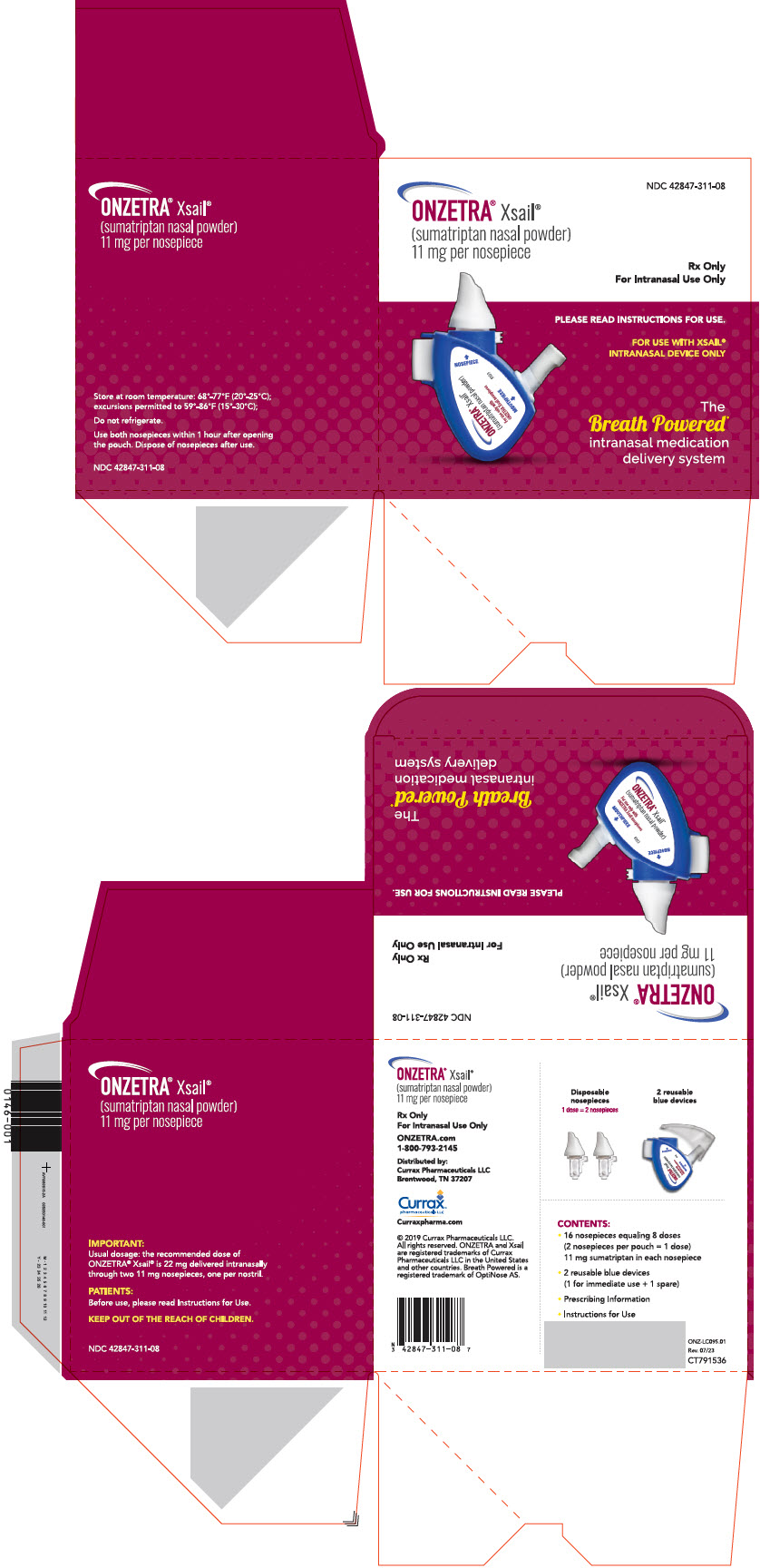 DRUG LABEL: Onzetra Xsail
NDC: 42847-311 | Form: CAPSULE
Manufacturer: Currax Pharmaceuticals LLC
Category: prescription | Type: HUMAN PRESCRIPTION DRUG LABEL
Date: 20240418

ACTIVE INGREDIENTS: SUMATRIPTAN SUCCINATE 11 mg/1 1

HIGHLIGHTS OF PRESCRIBING INFORMATION

These highlights do not include all the information needed to use ONZETRA Xsail safely and effectively. See full prescribing information for ONZETRA Xsail.
ONZETRA® Xsail® (sumatriptan nasal powder)
Initial U.S. Approval: 1992

1 INDICATIONS AND USAGE

ONZETRA Xsail is a serotonin 5-HT1B/1D receptor agonist (triptan) indicated for the acute treatment of migraine with or without aura in adults (1).

Limitations of Use

- Use only if a clear diagnosis of migraine headache has been established (1)
- Not indicated for the prophylactic therapy of migraine attacks (1)
- Not indicated for the treatment of cluster headache (1)

2 DOSAGE AND ADMINISTRATION

- Recommended dose: 22 mg, administered by use of one nosepiece (11 mg) in each nostril (2.1)
- Maximum dose in a 24-hour period should not exceed two doses (44 mg) separated by at least 2 hours (2.1)

3 DOSAGE FORMS AND STRENGTHS

- Capsule in disposable nosepiece: 11 mg sumatriptan as the succinate salt.
- For use with the Xsail breath-powered delivery device only.

4 CONTRAINDICATIONS

- History of coronary artery disease (CAD) or coronary vasospasm (4)
- Wolff-Parkinson-White syndrome or other cardiac accessory conduction pathway disorders (4)
- History of stroke, transient ischemic attack, or hemiplegic or basilar migraine (4)
- Peripheral vascular disease (4)
- Ischemic bowel disease (4)
- Uncontrolled hypertension (4)
- Recent (within 24 hours) use of another 5-HT1 agonist (e.g., another triptan) or of an ergotamine-containing medication (4)
- Concurrent or recent (past 2 weeks) use of monoamine oxidase-A inhibitor (4)
- Hypersensitivity to sumatriptan (angioedema and anaphylaxis seen) (4)
- Severe hepatic impairment (4)

5 WARNINGS AND PRECAUTIONS

- Myocardial ischemia/infarction and Prinzmetal's angina: Perform cardiac evaluation in patients with multiple cardiovascular risk factors (5.1)
- Arrhythmias: Discontinue ONZETRA Xsail if occurs (5.2)
- Chest/throat/neck/jaw pain, tightness, pressure, or heaviness: Generally not myocardial ischemia; evaluate high risk patients for CAD (5.3)
- Cerebral hemorrhage, subarachnoid hemorrhage, and stroke: Discontinue ONZETRA Xsail if occurs (5.4)
- Gastrointestinal ischemia and infarction events, peripheral vasospastic reactions: Discontinue ONZETRA Xsail if occurs (5.5)
- Medication overuse headache: Detoxification may be necessary (5.6)
- Serotonin syndrome: Discontinue ONZETRA Xsail if occurs (5.7)
- Seizures: Use with caution in patients with epilepsy or a lowered seizure threshold (5.10)

6 ADVERSE REACTIONS

In controlled studies with ONZETRA Xsail, the most common adverse reactions (incidence of ≥ 2% and greater than placebo) were abnormal taste, nasal discomfort, rhinorrhea, and rhinitis (6.1)

To report SUSPECTED ADVERSE REACTIONS, contact Currax Pharmaceuticals LLC at 1-800-793-2145 or FDA at 1-800-FDA-1088 or www.fda.gov/medwatch.

8 USE IN SPECIFIC POPULATIONS

- Pregnancy: Based on animal data, may cause fetal harm (8.1)

FULL PRESCRIBING INFORMATION

1 INDICATIONS AND USAGE

ONZETRA® Xsail® is indicated for the acute treatment of migraine with or without aura in adults.

Limitations of Use

- Use only if a clear diagnosis of migraine has been established. If a patient has no response to the first migraine attack treated with ONZETRA Xsail, reconsider the diagnosis of migraine before treatment of subsequent attacks with ONZETRA Xsail.
- ONZETRA Xsail is not indicated for the prevention of migraine attacks.
- Safety and effectiveness of ONZETRA Xsail have not been established for the treatment of cluster headache.

2 DOSAGE AND ADMINISTRATION

2.1 Dosing Information

The recommended dosage of ONZETRA is 22 mg of sumatriptan nasal powder (2 nosepieces), administered using the Xsail breath-powered delivery device. If the migraine has not resolved by 2 hours after taking ONZETRA Xsail, or returns after a transient improvement, a second dose of 22 mg may be administered at least 2 hours after the first dose. The maximum recommended dose that may be given in 24 hours is two doses of ONZETRA Xsail (44 mg/4 nosepieces) or one dose of ONZETRA Xsail and one dose of another sumatriptan product, separated by at least 2 hours. The safety of treating an average of more than 4 headaches in a 30 day period has not been established.

2.2 Administration Instructions

The recommended dose of 22 mg is administered by using one 11 mg nosepiece in each nostril [see Patient Counseling Information (17)]. For administration of ONZETRA Xsail, the patient removes the clear device cap from the reusable delivery device, then removes a disposable nosepiece from its foil pouch and clicks the nosepiece into the device body. The patient then fully presses and promptly releases the white piercing button on the device body to pierce the capsule inside the nosepiece. The white piercing button should only be pressed once and released prior to administration to each nostril. The nosepiece is then inserted into the nostril so that it makes a tight seal. Keeping the nosepiece in the nose, the device is rotated to place the mouthpiece into the mouth. The patient blows forcefully through the mouthpiece to deliver the sumatriptan powder into the nasal cavity. Vibration (e.g., a rattling noise) may occur, and indicates that the patient is blowing forcefully, as directed. Once the medication in the first nosepiece has been administered, the patient removes and discards the nosepiece. The same process must then be repeated using a second 11 mg nosepiece into the other nostril to administer the remainder of the total recommended 22 mg dose [see Patient Counseling Information (17)].

3 DOSAGE FORMS AND STRENGTHS

ONZETRA Xsail is supplied as a disposable nosepiece containing a capsule and a reusable delivery device body. Each capsule contains 11 mg sumatriptan base (equivalent to 15.4 mg of sumatriptan succinate nasal powder) in a clear, hypromellose capsule with 825 printed on one side.

4 CONTRAINDICATIONS

ONZETRA Xsail is contraindicated in patients with:

- Ischemic coronary artery disease (CAD) (e.g., angina pectoris, history of myocardial infarction, or silent ischemia) or coronary artery vasospasm, including Prinzmetal's angina or in patients with other significant underlying cardiovascular diseases [see Warnings and Precautions (5.1)].
- Wolff-Parkinson-White Syndrome or arrhythmias associated with other cardiac accessory conduction pathway disorders [see Warnings and Precautions (5.2)].
- History of stroke, transient ischemic attack (TIA), or history of hemiplegic or basilar migraine because these patients are at a higher risk of stroke [see Warnings and Precautions (5.4)].
- Peripheral vascular disease [see Warnings and Precautions (5.5)].
- Ischemic bowel disease [see Warnings and Precautions (5.5)].
- Uncontrolled hypertension [see Warnings and Precautions (5.8)].
- Recent use (i.e., within 24 hours) of ergotamine-containing medication, ergot-type medication (such as dihydroergotamine or methysergide), or another 5-hydroxytryptamine1 (5-HT1) agonist [see Drug Interactions (7.1 and 7.3)].
- Concurrent administration of an MAO-A inhibitor or recent use (within 2 weeks) of an MAO-A inhibitor [see Drug Interactions (7.2) and Clinical Pharmacology (12.3)].
- Hypersensitivity to sumatriptan (angioedema and anaphylaxis seen) [see Warnings and Precautions (5.9)].
- Severe hepatic impairment [see Clinical Pharmacology (12.3)]

5 WARNINGS AND PRECAUTIONS

5.1 Myocardial Ischemia, Myocardial Infarction, and Prinzmetal's Angina

The use of ONZETRA Xsail is contraindicated in patients with ischemic or vasospastic CAD. There have been rare reports of serious cardiac adverse reactions, including acute myocardial infarction, occurring within a few hours following administration of sumatriptan. Some of these reactions occurred in patients without known CAD. 5-HT1 agonists, including ONZETRA Xsail, may cause coronary artery vasospasm (Prinzmetal's angina), even in patients without a history of CAD.

Perform a cardiovascular evaluation in triptan-naïve patients who have multiple cardiovascular risk factors (e.g., increased age, diabetes, hypertension, smoking, obesity, strong family history of CAD) prior to receiving ONZETRA Xsail. If there is evidence of CAD or coronary artery vasospasm, ONZETRA Xsail is contraindicated. For patients with multiple cardiovascular risk factors who have a negative cardiovascular evaluation, consider administering the first dose of ONZETRA Xsail in a medically supervised setting and performing an electrocardiogram (ECG) immediately following administration of ONZETRA Xsail. For such patients, consider periodic cardiovascular evaluation in intermittent long-term users of ONZETRA Xsail.

5.2 Arrhythmias

Life-threatening disturbances of cardiac rhythm, including ventricular tachycardia and ventricular fibrillation leading to death, have been reported within a few hours following the administration of 5-HT1 agonists. Discontinue ONZETRA Xsail if these disturbances occur. ONZETRA Xsail is contraindicated in patients with Wolff-Parkinson-White syndrome or arrhythmias associated with other cardiac accessory conduction pathway disorders.

5.3 Chest, Throat, Neck, and/or Jaw Pain/Tightness/Pressure

Sensations of tightness, pain, pressure, and heaviness in the chest, throat, neck, and jaw commonly occur after treatment with 5-HT1 agonists including other products containing sumatriptan and are usually non-cardiac in origin. However, perform a cardiac evaluation if these patients are at high cardiac risk. The use of ONZETRA Xsail is contraindicated in patients with known CAD and those with Prinzmetal's variant angina.

5.4 Cerebrovascular Events

Cerebral hemorrhage, subarachnoid hemorrhage, stroke, and other cerebrovascular events have occurred in patients treated with 5-HT1 agonists including other products containing sumatriptan, and some have resulted in fatalities. In a number of cases, it appears possible that the cerebrovascular events were primary, the 5-HT1 agonist having been administered in the incorrect belief that the symptoms experienced were a consequence of migraine when they were not. Patients with migraine may be at increased risk of certain cerebrovascular events (e.g., stroke, hemorrhage, TIA). ONZETRA Xsail is contraindicated in patients with a history of stroke or TIA. Discontinue ONZETRA Xsail if a cerebrovascular event occurs.

Before treating headaches in patients not previously diagnosed as migraineurs, and in migraineurs who present with atypical symptoms, exclude other potentially serious neurological conditions.

5.5 Other Vasospasm Reactions

5-HT1 agonists, including ONZETRA Xsail, may cause non-coronary vasospastic reactions, such as peripheral vascular ischemia, gastrointestinal vascular ischemia and infarction (presenting with abdominal pain and bloody diarrhea), splenic infarction, and Raynaud's syndrome. In patients who experience symptoms or signs suggestive of a non-coronary vasospastic reaction following the use of any 5-HT1 agonist, rule out a vasospastic reaction before using ONZETRA Xsail.

Transient and permanent blindness and significant partial vision loss have been reported with the use of 5-HT1 agonists including sumatriptan. Since visual disorders may be part of a migraine attack, a causal relationship between these events and the use of 5-HT1 agonists have not been clearly established.

5.6 Medication Overuse Headache

Overuse of acute migraine drugs (e.g., ergotamine, triptans, opioids, nonsteroidal anti-inflammatory drugs or combinations of these drugs for 10 or more days per month) may lead to exacerbation of headache (medication overuse headache). Medication overuse headache may present as migraine-like daily headaches or as a marked increase in frequency of migraine attacks. Detoxification of patients, including withdrawal of the overused drugs, and treatment of withdrawal symptoms (which often includes a transient worsening of headache) may be necessary.

5.7 Serotonin Syndrome

Serotonin syndrome may occur with triptans, including ONZETRA Xsail, particularly during co-administration with selective serotonin reuptake inhibitors (SSRIs), serotonin norepinephrine reuptake inhibitors (SNRIs), tricyclic antidepressants (TCAs), and MAO inhibitors [see Drug Interactions (7.4)]. Serotonin syndrome symptoms may include mental status changes (e.g., agitation, hallucinations, coma), autonomic instability (e.g., tachycardia, labile blood pressure, hyperthermia), neuromuscular abnormalities (e.g., hyperreflexia, incoordination), and/or gastrointestinal symptoms (e.g., nausea, vomiting, diarrhea). The onset of symptoms usually occurs within minutes to hours of receiving a new or a greater dose of a serotonergic medication. Discontinue ONZETRA Xsail if serotonin syndrome is suspected.

5.8 Increase in Blood Pressure

Significant elevation in blood pressure, including hypertensive crisis with acute impairment of organ systems, has been reported on rare occasions in patients treated with 5-HT1 agonists, including patients without a history of hypertension. Monitor blood pressure in patients treated with ONZETRA Xsail. ONZETRA Xsail is contraindicated in patients with uncontrolled hypertension.

5.9 Hypersensitivity Reactions

Hypersensitivity reactions, including angioedema and anaphylaxis, have occurred in patients receiving sumatriptan. Such reactions can be life-threatening or fatal. In general, anaphylactic reactions to drugs are more likely to occur in individuals with a history of sensitivity to multiple allergens. ONZETRA Xsail is contraindicated in patients with a history of hypersensitivity reaction to sumatriptan.

5.10 Seizures

Seizures have been reported following administration of sumatriptan. Some have occurred in patients with either a history of seizures or concurrent conditions predisposing to seizures. There are also reports in patients where no such predisposing factors are apparent. ONZETRA Xsail should be used with caution in patients with a history of epilepsy or conditions associated with a lowered seizure threshold.

6 ADVERSE REACTIONS

The following serious adverse reactions are discussed in more detail in other sections of the prescribing information:

- Myocardial ischemia, myocardial infarction, and Prinzmetal's angina [see Warnings and Precautions (5.1)]
- Arrhythmias [see Warnings and Precautions (5.2)]
- Chest, throat, neck and/or jaw pain/tightness/pressure [see Warnings and Precautions (5.3)]
- Cerebrovascular events [see Warnings and Precautions (5.4)]
- Other vasospasm reactions [see Warnings and Precautions (5.5)]
- Medication overuse headache [see Warnings and Precautions (5.6)]
- Serotonin syndrome [see Warnings and Precautions (5.7)]
- Increase in blood pressure [see Warnings and Precautions (5.8)]
- Hypersensitivity reactions [see Contraindications (4) and Warnings and Precautions (5.9)]
- Seizures [see Warnings and Precautions (5.10)]

6.1 Clinical Trials Experience

Because clinical trials are conducted under widely varying conditions, adverse reaction rates observed in the clinical trials of a drug cannot be directly compared to the rates in the clinical trials of another drug, and may not reflect the rates observed in practice.

Table 1 lists adverse reactions that occurred in 2 placebo-controlled clinical trials in 301 patients with migraine who took at least 1 dose of ONZETRA Xsail or placebo. Only adverse reactions that occurred at a frequency of 2% or more with ONZETRA Xsail and that occurred at a frequency greater than the placebo group are included in Table 1.

Table 1: Adverse Reactions Reported by at Least 2% of Patients in 2 Controlled Migraine Trials
 | Percent of Patients Reporting
Adverse Reaction | ONZETRA N=151 | Placebo N=150
Abnormal Taste | 20 | 3
Nasal Discomfort | 11 [Limited examinations of the nose and throat did not reveal any clinically noticeable injury in these patients.] | 1
Rhinorrhea | 5 | 2
Rhinitis | 2 | 0

There is insufficient data with ONZETRA Xsail to assess the impact of age, gender, and race on adverse effects.

6.2 Postmarketing Experience

The following adverse reaction has been identified during post approval use of ONZETRA Xsail. Because this reaction is reported voluntarily from a population of uncertain size, it is not always possible to reliably estimate its frequency or establish a causal relationship to drug exposure.

Epistaxis has been identified during post approval use of ONZETRA Xsail as an adverse reaction.

7 DRUG INTERACTIONS

7.1 Ergot-Containing Drugs

Ergot-containing drugs have been reported to cause prolonged vasospastic reactions. Because these effects may be additive, use of ergotamine containing or ergot-type medications (like dihydroergotamine or methysergide) and ONZETRA Xsail within 24 hours of each other is contraindicated.

7.2 Monoamine Oxidase Inhibitors

MAO-A inhibitors increase systemic exposure by up to 7-fold. Therefore, the use of ONZETRA Xsail in patients receiving MAO-A inhibitors is contraindicated [see Clinical Pharmacology (12.3)].

7.3 Other 5-HT1 Agonists

Because their vasospastic effects may be additive, co-administration of ONZETRA Xsail and other 5-HT1 agonists (e.g., triptans) within 24 hours of each other is contraindicated.

7.4 Selective Serotonin Reuptake Inhibitors/Serotonin Norepinephrine Reuptake Inhibitors and Serotonin Syndrome

Cases of serotonin syndrome have been reported during co-administration of triptans and SSRIs, SNRIs, TCAs, and MAO inhibitors [see Warnings and Precautions (5.7)].

8 USE IN SPECIFIC POPULATIONS

8.1 Pregnancy

Risk Summary

Data from a prospective pregnancy exposure registry and epidemiological studies of pregnant women have not detected an increased frequency of birth defects or a consistent pattern of birth defects among women exposed to sumatriptan compared with the general population (see Data). In developmental toxicity studies in rats and rabbits, oral administration of sumatriptan to pregnant animals was associated with embryolethality, fetal abnormalities, and pup mortality. When administered by the intravenous route to pregnant rabbits, sumatriptan was embryolethal (see Data).

In the U.S. general population, the estimated background risk of major birth defects and of miscarriage in clinically recognized pregnancies is 2% to 4% and 15% to 20%, respectively. The reported rate of major birth defects among deliveries to women with migraine ranged from 2.2% to 2.9%, and the reported rate of miscarriage was 17%, which were similar to rates reported in women without migraine.

Clinical Considerations

Disease-Associated Maternal and/or Embryo/Fetal Risk: Several studies have suggested that women with migraine may be at increased risk of preeclampsia and gestational hypertension during pregnancy.

Data

Human Data: The Sumatriptan/Naratriptan/Treximet (sumatriptan and naproxen sodium) Pregnancy Registry, a population-based international prospective study, collected data for sumatriptan from January 1996 to September 2012. The Registry documented outcomes of 626 infants and fetuses exposed to sumatriptan during pregnancy (528 with earliest exposure during the first trimester, 78 during the second trimester, 16 during the third trimester, and 4 unknown). The occurrence of major birth defects (excluding fetal deaths and induced abortions without reported defects and all spontaneous pregnancy losses) during first-trimester exposure to sumatriptan was 4.2% (20/478 [95% CI: 2.6% to 6.5%]) and during any trimester of exposure was 4.2% (24/576 [95% CI: 2.7% to 6.2%]). The sample size in this study had 80% power to detect at least a 1.73- to 1.91-fold increase in the rate of major malformations. The number of exposed pregnancy outcomes accumulated during the registry was insufficient to support definitive conclusions about overall malformation risk or to support comparisons of the frequencies of specific birth defects. Of the 20 infants with reported birth defects after exposure to sumatriptan in the first trimester, 4 infants had ventricular septal defects, including one infant who was exposed to both sumatriptan and naratriptan, and 3 infants had pyloric stenosis. No other birth defect was reported for more than 2 infants in this group.

In a study using data from the Swedish Medical Birth Register, live births to women who reported using triptans or ergots during pregnancy were compared with those of women who did not. Of the 2,257 births with first-trimester exposure to sumatriptan, 107 infants were born with malformations (relative risk 0.99 [95% CI: 0.91 to 1.21]). A study using linked data from the Medical Birth Registry of Norway to the Norwegian Prescription Database compared pregnancy outcomes in women who redeemed prescriptions for triptans during pregnancy, as well as a migraine disease comparison group who redeemed prescriptions for sumatriptan before pregnancy only, compared with a population control group. Of the 415 women who redeemed prescriptions for sumatriptan during the first trimester, 15 had infants with major congenital malformations (OR 1.16 [95% CI: 0.69 to 1.94]) while for the 364 women who redeemed prescriptions for sumatriptan before, but not during, pregnancy, 20 had infants with major congenital malformations (OR 1.83 [95% CI: 1.17 to 2.88]), each compared with the population comparison group. Additional smaller observational studies evaluating use of sumatriptan during pregnancy have not suggested an increased risk of teratogenicity.

Animal Data: Oral administration of sumatriptan to pregnant rats during the period of organogenesis resulted in an increased incidence of fetal blood vessel (cervicothoracic and umbilical) abnormalities. The highest no-effect dose for embryofetal developmental toxicity in rats was 60 mg/kg/day. Oral administration of sumatriptan to pregnant rabbits during the period of organogenesis resulted in increased incidences of embryolethality and fetal cervicothoracic vascular and skeletal abnormalities. Intravenous administration of sumatriptan to pregnant rabbits during the period of organogenesis resulted in an increased incidence of embryolethality. The highest oral and intravenous no-effect doses for developmental toxicity in rabbits were 15 and 0.75 mg/kg/day, respectively.

Oral administration of sumatriptan to rats prior to and throughout gestation resulted in embryofetal toxicity (decreased body weight, decreased ossification, increased incidence of skeletal abnormalities). The highest no-effect dose was 50 mg/kg/day. In offspring of pregnant rats treated orally with sumatriptan during organogenesis, there was a decrease in pup survival. The highest no-effect dose for this effect was 60 mg/kg/day. Oral treatment of pregnant rats with sumatriptan during the latter part of gestation and throughout lactation resulted in a decrease in pup survival. The highest no-effect dose for this finding was 100 mg/kg/day.

8.2 Lactation

Risk Summary

Sumatriptan is excreted in human milk following subcutaneous administration (see Data). There is no information regarding sumatriptan concentrations in milk from lactating women following administration of ONZETRA Xsail. There are no data on the effects of sumatriptan on the breastfed infant or the effects of sumatriptan on milk production.

The developmental and health benefits of breastfeeding should be considered along with the mother's clinical need for ONZETRA Xsail and any potential adverse effects on the breastfed infant from sumatriptan or from the underlying maternal condition.

Clinical Considerations

Infant exposure to sumatriptan can be minimized by avoiding breastfeeding for 12 hours after treatment with ONZETRA Xsail.

Data

Following subcutaneous administration of a 6-mg dose of sumatriptan injection in 5 lactating volunteers, sumatriptan was present in milk.

8.4 Pediatric Use

Safety and effectiveness has not been established in pediatric patients younger than 18 years of age.

Two controlled clinical trials evaluated sumatriptan nasal spray (5 to 20 mg) in 1,248 adolescent migraineurs aged 12 to 17 years who treated a single attack. The trials did not establish the efficacy of sumatriptan nasal spray compared with placebo in the treatment of migraine in adolescents. Adverse reactions observed in these clinical trials were similar in nature to those reported in clinical trials in adults.

Five controlled clinical trials (2 single-attack studies, 3 multiple-attack studies) evaluating oral sumatriptan (25 to 100 mg) in pediatric patients aged 12 to 17 years enrolled a total of 701 adolescent migraineurs. These studies did not establish the efficacy of oral sumatriptan compared to placebo in the treatment of migraine in adolescents. Adverse reactions observed in these clinical trials were similar in nature to those reported in clinical trials in adults. The frequency of all adverse reactions in these patients appeared to be both dose- and age-dependent, with younger patients reporting reactions more commonly than older adolescents.

Postmarketing experience documents that serious adverse reactions have occurred in the pediatric population after use of subcutaneous, oral, and/or intranasal sumatriptan. These reports include reactions similar in nature to those reported rarely in adults, including stroke, visual loss, and death. A myocardial infarction has been reported in a 14-year-old male following the use of oral sumatriptan; clinical signs occurred within 1 day of drug administration. Clinical data to determine the frequency of serious adverse reactions in pediatric patients who might receive subcutaneous, oral, or nasal sumatriptan are not presently available.

8.5 Geriatric Use

Clinical trials of ONZETRA Xsail did not include sufficient numbers of subjects aged 65 and over to determine whether they respond differently from younger subjects. Other reported clinical experience with subcutaneous, oral, and liquid nasal spray sumatriptan has not identified differences in responses between the elderly and younger patients. In general, treatment for an elderly patient should be cautious, reflecting the greater frequency of decreased or abnormal hepatic function, renal function, or cardiac function, more pronounced blood pressure increases, higher risks for unrecognized CAD, and/or concomitant disease or other drug therapy.

A cardiovascular evaluation is recommended for geriatric patients who have other cardiovascular risk factors (e.g., diabetes, hypertension, smoking, obesity, strong family history of CAD) prior to receiving ONZETRA Xsail [see Warnings and Precautions (5.1)].

8.6 Hepatic Impairment

The clearance of oral sumatriptan was reduced in patients with moderate hepatic impairment [see Clinical Pharmacology (12.3)]. Similar changes can be expected following intranasal administration. The effect of severe hepatic impairment was NOT evaluated using oral formulation. The use of ONZETRA Xsail in patients with severe hepatic impairment is contraindicated [see Contraindications (4)].

10 OVERDOSAGE

In clinical trials, the highest single doses of sumatriptan nasal spray administered without significant reactions were 40 mg to 12 volunteers and 40 mg to 85 subjects with migraine, which is twice the highest single recommended dose. In addition, 12 volunteers were administered a total daily dose of 60 mg (20 mg 3 times daily) for 3.5 days without significant adverse reactions.

Overdose in animals has been fatal and has been heralded by convulsions, tremor, paralysis, inactivity, ptosis, erythema of the extremities, abnormal respiration, cyanosis, ataxia, mydriasis, salivation, and lacrimation.

The elimination half-life of ONZETRA Xsail is about 3 hours [see Clinical Pharmacology (12.3)], and therefore monitoring of patients after overdose with ONZETRA Xsail should continue for at least 15 hours or while symptoms persist.

It is unknown what effect hemodialysis or peritoneal dialysis has on the serum concentrations of sumatriptan.

11 DESCRIPTION

ONZETRA Xsail (sumatriptan nasal powder) uses a disposable, single use nosepiece which is attached by the patient to a delivery device body which has a mouthpiece and a piercing mechanism. The nosepiece contains a hypromellose capsule filled with 11 mg sumatriptan base (as 15.4 mg of sumatriptan succinate) in a dry powder form. Two nosepieces comprise a single 22 mg dose. ONZETRA is for nasal administration with the Xsail device only.

The active component of ONZETRA Xsail is sumatriptan, a selective 5-hydroxy-tryptamine receptor subtype 1 (5-HT1) agonist (triptan), as the succinate salt. Sumatriptan succinate is chemically designated as 3-[2-(dimethylamino)ethyl]-N-methyl-indole-5-methanesulfonamide succinate (1:1), and it has the following structure:

The empirical formula is C14H21N3O2S ∙ C4H6O4, representing a molecular weight of 413.5.

Sumatriptan succinate is a white to off-white powder that is readily soluble in water and in saline.

The ONZETRA Xsail breath-powered delivery device is used to deliver the dry powder contained in the disposable nosepiece (in a capsule) into the nostril using breath exhaled into the device. The Xsail delivery device has a flexible mouthpiece to adjust to individual anatomic variations. Under standardized in vitro testing, the Xsail device delivers a mean of 10 mg sumatriptan per nosepiece when tested at a flow rate of 30 L/min for 4 seconds (2 L total). The amount of sumatriptan delivered to the nasal cavity will depend on patient factors such as expiratory flow. Delivered dose was measured in patients with migraine headache treated in clinical trials to evaluate the efficacy of the product. In these trials, each nosepiece delivered an average dose of 7.5-8.1 mg, providing a total dose of 15-16.2 mg per treatment episode from two nosepieces.

12 CLINICAL PHARMACOLOGY

12.1 Mechanism of Action

Sumatriptan binds with high affinity to human cloned 5-HT1B/1D receptors. Sumatriptan presumably exerts its therapeutic effects in the treatment of migraine headache through agonist effects at the 5-HT1B/1D receptors on intracranial blood vessels and sensory nerves of the trigeminal system, which result in cranial vessel constriction and inhibition of pro-inflammatory neuropeptide release.

12.2 Pharmacodynamics

Blood Pressure

Significant elevation in blood pressure, including hypertensive crisis, has been reported in patients treated with sumatriptan, with and without a history of hypertension [see Warnings and Precautions (5.8)].

Peripheral (Small) Arteries

In healthy volunteers (N = 18), a trial evaluating the effects of sumatriptan injection on peripheral (small vessel) arterial reactivity failed to detect a clinically significant increase in peripheral resistance.

Heart Rate

Transient increases in blood pressure observed in some patients in clinical studies carried out during development of sumatriptan as a treatment for migraine were not accompanied by any clinically significant changes in heart rate.

12.3 Pharmacokinetics

Absorption and Bioavailability

The mean maximum concentration (Cmax) following a 22 mg nasal dose of ONZETRA Xsail was 21 ng/mL (range: 9 to 61 ng/mL), and the AUC0-∞ was 65 ng∙hr/ml (range: 40 to 107 ng/mL). Peak plasma concentration (Tmax) was achieved on average 45 minutes (range: 10 minutes to 2 hours) following ONZETRA Xsail administration. The bioavailability of ONZETRA relative to subcutaneous injection was approximately 19%, primarily due to pre-systemic metabolism and partly due to incomplete absorption. Sumatriptan bioavailability following liquid nasal spray administration is 14%, similar to that after oral administration (15%).

Distribution

Protein binding of sumatriptan, determined by equilibrium dialysis over the concentration range of 10 to 1000 ng/mL, is approximately 14% to 21%. The effect of sumatriptan on the protein binding of other drugs has not been evaluated. The apparent volume of distribution is 2.7 L/kg.

Metabolism

In vitro studies with human microsomes suggest that sumatriptan is metabolized by MAO (predominately A isoenzyme). Most of a radiolabeled dose of sumatriptan excreted in the urine is the major metabolite indole acetic acid (IAA) or the IAA glucuronide, both of which are inactive.

Elimination

The elimination half-life of sumatriptan administered as a nasal powder by the Xsail device is approximately 3 hours, similar to the half-life seen with sumatriptan nasal spray. Only 3% of a nasal spray dose is excreted in the urine as unchanged sumatriptan; 42% of a nasal spray dose is excreted as the major metabolite, the indole acetic acid analogue of sumatriptan. The total plasma clearance of the nasal spray is approximately 1200 mL/min.

Specific Populations

Age

The pharmacokinetics of oral sumatriptan in the elderly (mean age: 72 years, 2 males and 4 females) and in patients with migraine (mean age: 38 years, 25 males and 155 females) were similar to that in healthy male subjects (mean age: 30 years). Intranasal sumatriptan has not been evaluated for age differences.

Race

The systemic clearance and Cmax of subcutaneous sumatriptan were similar in black (n=34) and Caucasian (n=38) healthy male subjects. Intranasal sumatriptan has not been evaluated for race differences.

Renal Impairment

The effect of renal impairment on the pharmacokinetics of sumatriptan has not been examined.

Hepatic Impairment

The effect of mild hepatic disease on the pharmacokinetics of sumatriptan has not been evaluated. Following oral administration, an approximately 70% increase in Cmax and AUC was observed in one small trial of patients with moderate liver impairment (n=8) matched for sex, age, and weight with healthy subjects (n=8). Similar changes can be expected following intranasal administration.

The pharmacokinetics of sumatriptan in patients with severe hepatic impairment has not been studied [see Contraindications (4)].

Drug Interaction Studies

Monoamine Oxidase-A Inhibitors

Treatment with MAO-A inhibitors generally leads to an increase of sumatriptan plasma levels [see Contraindications (4) and Drug Interactions (7.2)]. MAO inhibitors interaction studies have not been performed with intranasal sumatriptan.

Due to gut and hepatic metabolic first-pass effects, the increase of systemic exposure after co-administration of an MAO-A inhibitor with oral sumatriptan is greater than after co-administration of the MAO inhibitors with subcutaneous sumatriptan. The effects of an MAO inhibitor on systemic exposure after intranasal sumatriptan would be expected to be greater than the effect after subcutaneous sumatriptan but smaller than the effect after oral sumatriptan because only swallowed drug would be subject to first-pass effects.

In a trial of 14 healthy females, pretreatment with an MAO-A inhibitor decreased the clearance of subcutaneous sumatriptan, resulting in a 2-fold increase in the area under the sumatriptan plasma concentration-time curve (AUC), corresponding to a 40% increase in elimination half-life.

A small study evaluating the effect of pretreatment with an MAO-A inhibitor on the bioavailability from a 25 mg oral sumatriptan tablet resulted in an approximately 7-fold increase in systemic exposure.

Xylometazoline

An in vivo drug interaction trial indicated that 3 drops of xylometazoline (0.1% w/v), a decongestant, administered 15 minutes prior to a 20 mg nasal spray dose of sumatriptan did not alter the pharmacokinetics of sumatriptan.

13 NONCLINICAL TOXICOLOGY

13.1 Carcinogenesis, Mutagenesis, Impairment of Fertility

Carcinogenesis

In carcinogenicity studies in mouse and rat in which sumatriptan was administered orally for 78 weeks and 104 weeks, respectively, there was no evidence in either species of an increase in tumors related to sumatriptan administration.

Carcinogenicity studies of sumatriptan using the nasal route have not been conducted.

Mutagenesis

Sumatriptan was negative in in vitro (bacterial reverse mutation [Ames], gene cell mutation in Chinese hamster V79/HGPRT, chromosomal aberration in human lymphocytes) and in vivo (rat micronucleus) assays.

Impairment of Fertility

When sumatriptan (5, 50, or 500 mg/kg/day) was administered orally to male and female rats prior to and throughout the mating period, there was a treatment-related decrease in fertility secondary to a decrease in mating in animals treated with doses greater than 5 mg/kg/day. It is not clear whether this finding was due to an effect on males or females or both.

When sumatriptan was administered by subcutaneous injection to male and female rats prior to and throughout the mating period, there was no evidence of impaired fertility at doses of up to 60 mg/kg/day.

Fertility studies of sumatriptan using the intranasal route have not been conducted.

13.2 Animal Toxicology and/or Pharmacology

Corneal Opacities

Dogs receiving oral sumatriptan developed corneal opacities and defects in the corneal epithelium. Corneal opacities were seen at the lowest dose tested, 2 mg/kg/day, and were present after 1 month of treatment. Defects in the corneal epithelium were noted in a 60-week study. Earlier examinations for these toxicities were not conducted, and no-effect doses were not established.

14 CLINICAL STUDIES

The efficacy of ONZETRA Xsail for the acute treatment of migraine with or without aura was established in a multicenter, randomized, double-blind, placebo-controlled study (Study 1).

Migraineurs enrolled in Study 1 were primarily female (84%) and Caucasian (86%), with a mean age of 42 years (range of 19 to 64). Patients were instructed to treat a moderate to severe migraine headache. Additional medications were allowed as rescue therapy beginning 2 hours after the initial treatment.

In Study 1, the proportion of patients who had headache relief defined as a reduction from moderate or severe pain to mild or no pain was assessed at 15, 30, 60, 90 minutes and 2, 24 and 48 hours after treatment with study drug. Associated symptoms of nausea, photophobia, and phonophobia were assessed as secondary endpoints. The proportion of patients who had no headache at 2 hours (120 minutes) was also assessed.

The percentage of patients achieving headache relief 2 hours after treatment was significantly greater in the ONZETRA Xsail 22 mg group compared to those who received placebo (see Table 2 and Figure 1). For patients with migraine-associated nausea, photophobia, and phonophobia at baseline, there was a lower incidence of these symptoms at 2 hours following administration of ONZETRA Xsail compared with placebo.

Table 2: Percentage of Patients With Headache Relief (Primary Efficacy Endpoint), with No Headache, No Nausea, No Photophobia, and No Phonophobia 2 hours Post Treatment with ONZETRA Xsail (Study 1)
2 hours post treatment | ONZETRA 22 mg (n=108) | Placebo (n=104)
Headache Relief | 68% [p<0.05 versus placebo] | 45%
No Headache | 34% | 17%
No Nausea | 82% | 79%
No Photophobia | 52% | 40%
No Phonophobia | 68% | 56%

Figure 1: Percentage of Patients with Headache Relief within 2 Hours with ONZETRA Xsail

The efficacy of ONZETRA Xsail was unaffected by presence of aura; duration of headache prior to treatment; gender, age, or weight of the subject; or concomitant use of common migraine prophylactic drugs (e.g., beta-blockers, calcium channel blockers, tricyclic antidepressants). There was insufficient data to assess the impact of race on efficacy.

16 HOW SUPPLIED/STORAGE AND HANDLING

16.1 How Supplied

ONZETRA Xsail is supplied as a disposable nosepiece containing a capsule and a reusable breath-powered delivery device body. Each capsule contains 11 mg sumatriptan base (equivalent to 15.4 mg of sumatriptan succinate nasal powder) in a clear, hypromellose capsule with 825 printed on one side.

ONZETRA Xsail is available in kits containing 8 doses.

The following table provides a description of the packaging configurations:

Description | Contents | NDC Code
8 Dose Kit | 8 pouches containing 2 nosepieces (22 mg sumatriptan) per pouch. Each nosepiece contains 11 mg sumatriptan 2 breath-powered delivery system bodies | 42847-311-08

16.2 Storage and Handling

Store at room temperature between 20°C to 25°C (68°F to 77°F), with excursions permitted between 15°C to 30°C (59°F to 86°F). Do not store in the refrigerator or freezer. Use nosepiece immediately after removing from foil pouch.

17 PATIENT COUNSELING INFORMATION

Advise the patient to read the FDA-approved patient labeling (Patient Information and Instructions for Use).

Only patients who are able to understand and follow the instructions should use ONZETRA Xsail.

Instructions on the proper use of ONZETRA Xsail from a physician or healthcare professional prior to administration for the first time may be helpful. For support, healthcare professionals and patients can call 1-800-793-2145 or see www.ONZETRA.com.

Risk of Myocardial Ischemia and/or Infarction, Prinzmetal's Angina, Other Vasospasm-Related Events, Arrhythmias, and Cerebrovascular Events

Inform patients that triptan medications, including ONZETRA Xsail, may cause serious cardiovascular side effects such as myocardial infarction or stroke, which may result in hospitalization and even death. Although serious cardiovascular events can occur without warning symptoms, patients should be alert for the signs and symptoms of chest pain, shortness of breath, irregular heartbeat, significant rise in blood pressure, weakness, and slurring of speech and should ask for medical advice if any indicative signs or symptoms are observed. Apprise patients of the importance of this follow-up [see Warnings and Precautions (5.1, 5.2, 5.3, 5.4, and 5.5)].

Hypersensitivity Reactions

Inform patients that anaphylactic reactions have occurred in patients receiving sumatriptan. Such reactions can be life-threatening or fatal. In general, anaphylactic reactions to drugs are more likely to occur in individuals with a history of sensitivity to multiple allergens [see Warnings and Precautions (5.9)].

Concomitant Use with Other Triptans and Ergot Medications

Inform patients that use of ONZETRA Xsail within 24 hours of another triptan or an ergot-type medication (including dihydroergotamine or methysergide) is contraindicated [see Contraindications (4) and Drug Interactions (7.1, 7.3)].

Serotonin Syndrome

Caution patients about the risk of serotonin syndrome with the use of ONZETRA Xsail or other triptans, particularly during combined use with SSRIs, SNRIs, TCAs, and MAO inhibitors [see Warnings and Precautions (5.7) and Drug Interactions (7.4)].

Medication Overuse Headache

Inform patients that use of acute migraine drugs for 10 or more days per month may lead to an exacerbation of headache and encourage patients to record headache frequency and drug use (e.g., by keeping a headache diary) [see Warnings and Precautions (5.6)].

Pregnancy

Advise patients to notify their healthcare provider if they become pregnant during treatment or plan to become pregnant [see Use in Specific Populations (8.1)].

Nursing Mothers

Advise patients to notify their healthcare provider if they are breastfeeding or plan to breastfeed [see Use in Specific Populations (8.2)].

Ability To Perform Complex Tasks

Treatment with sumatriptan may cause somnolence and dizziness; instruct patients to evaluate their ability to perform complex tasks during migraine attacks and after administration of ONZETRA Xsail.

Local Irritation

Inform patients that they may experience local irritation of their nose and throat. The symptoms will generally resolve in less than 2 hours.

How to Use ONZETRA Xsail with the breath powered device

Provide patients with instructions on the proper use of ONZETRA Xsail with the breath powered device.

Advise patients that use of the breath powered device is for ONZETRA Xsail only. No other product or substance is approved for use in the breath powered device.

Advise patients to remove a disposable nosepiece from the foil pouch, remove the clear device cap from the reusable device, and click the nosepiece into the device body.

Advise the patient to fully press and release the white piercing button on the device body to pierce the capsule inside the nosepiece. Instruct the patient to press the white piercing button only once.

Advise the patient to insert the nosepiece into the nostril so that it makes a tight seal. The device is then rotated and the mouthpiece inserted between the lips.

Instruct the patient to blow forcefully through the mouthpiece to deliver the sumatriptan powder into the nasal cavity. Vibration (e.g., a rattling noise) may occur, and indicates that the patient is blowing forcefully, as directed.

Advise the patient to remove and discard the nosepiece in the trash once the medication has been administered.

Instruct the patient to follow the same process using a second nosepiece in the other nostril to administer the remainder of the total recommended dose.

ONZETRA and Xsail are registered trademarks of Currax™ Pharmaceuticals LLC in the United States and other countries

Distributed by:
Currax™ Pharmaceuticals LLC
Brentwood, TN 37027

©2024 Currax™ Pharmaceuticals LLC All rights reserved

Patient Information ONZETRA® (On ze' trah) Xsail® (Eks'-seil) (sumatriptan nasal powder) 11 mg

Read this Patient Information before you start using ONZETRA Xsail and each time you get a refill. There may be new information. This information does not take the place of talking with your healthcare provider about your medical condition or treatment.

What is the most important information I should know about ONZETRA Xsail?

ONZETRA Xsail can cause serious side effects, including:

Heart attack and other heart problems. Heart problems may lead to death.

Stop taking ONZETRA Xsail and get emergency medical help right away if you have any of the following symptoms of a heart attack:

- discomfort in the center of your chest that lasts for more than a few minutes, or that goes away and comes back
- severe tightness, pain, pressure, or heaviness in your chest, throat, neck, or jaw
- pain or discomfort in your arms, back, neck, jaw or stomach
- shortness of breath with or without chest discomfort
- breaking out in a cold sweat
- nausea or vomiting
- feeling lightheaded

ONZETRA Xsail is not for people with risk factors for heart disease unless a heart exam is done and shows no problem. You have a higher risk for heart disease if you:

- have high blood pressure
- have high cholesterol levels
- smoke
- are overweight
- have diabetes
- have a family history of heart disease

What is ONZETRA Xsail?

ONZETRA Xsail is a prescription medicine used to treat acute migraine headaches with or without aura in adults.

ONZETRA Xsail is not used to treat other types of headaches such as hemiplegic migraines (that make you unable to move on one side of your body) or basilar migraines (rare form of migraine with aura).

ONZETRA Xsail is not used to prevent or decrease the number of migraine headaches you have.

It is not known if ONZETRA Xsail is safe and effective to treat cluster headaches.

It is not known if ONZETRA Xsail is safe and effective in children under 18 years of age.

Who should not use ONZETRA Xsail?

Do not use ONZETRA Xsail if you have:

- an allergy to sumatriptan
- heart problems or history of heart problems
- narrowing of blood vessels to your legs, arms, stomach or kidney (peripheral vascular disease)
- uncontrolled high blood pressure
- severe liver problems
- hemiplegic migraines or basilar migraines. If you are not sure if you have these types of migraines, ask your healthcare provider.
- had a stroke, transient ischemic attacks (TIAs) or problems with your blood circulation
- taken any of the following medicines in the last 24 hours:
  - almotriptan (AXERT®)
  - eletriptan (RELPAX®)
  - frovatriptan (FROVA®)
  - naratriptan (AMERGE®)
  - rizatriptan (MAXALT®, MAXALT-MLT®)
  - zolmitriptan (ZOMIG®, ZOMIG-ZMT®, ZOMIG® NASAL SPRAY)
  - sumatriptan (IMITREX®, IMITREX® NASAL SPRAY, IMITREX® INJECTION)
  - sumatriptan and naproxen (TREXIMET®)
  - sumatriptan (SUMAVEL® DOSE PRO® INJECTION)
  - sumatriptan (ALSUMA®)
  - sumatriptan (ZECUITY® TRANSDERMAL PATCH)
  - ergotamines (CAFERGOT®, ERGOMAR®, MIGERGOT®)
  - dihydroergotamine (D.H.E. 45®, MIGRANAL®)
    Ask your healthcare provider if you are not sure if your medicine is listed above.

What should I tell my healthcare provider before taking ONZETRA Xsail?

Before you use ONZETRA Xsail, tell your healthcare provider about all of your medical conditions, including if you:

- have high blood pressure
- have high cholesterol
- have diabetes
- smoke
- are overweight
- have heart problems or a family history of heart problems or stroke
- have kidney problems
- have liver problems
- have had epilepsy or seizures
- are not using effective birth control
- are pregnant or plan to become pregnant. It is not known if ONZETRA Xsail can harm your unborn baby.
- are breastfeeding or plan to breastfeed. ONZETRA Xsail passes into your breast milk. It is not known if this can harm your baby. Talk with your healthcare provider about the best way to feed your baby if you use ONZETRA Xsail.

Tell your healthcare provider about all the medicines you take, including prescription and nonprescription medicines, vitamins and herbal supplements.

ONZETRA Xsail and certain other medicines can affect each other, causing serious side effects.

Especially tell your healthcare provider if you take anti-depressant medicines called:

- selective serotonin reuptake inhibitors (SSRIs)
- serotonin norepinephrine reuptake inhibitors (SNRIs)
- tricyclic antidepressants (TCAs)
- monoamine oxidase inhibitors (MAOIs)

Ask your healthcare provider or pharmacist for a list of these medicines if you are not sure.

Know the medicines you take. Keep a list of them to show your healthcare provider or pharmacist when you get a new medicine.

How should I use ONZETRA Xsail?

Before using ONZETRA Xsail, read the Patient Instructions for Use.

- Certain people should use their first dose of ONZETRA Xsail in their healthcare provider's office or in another medical setting. Ask your healthcare provider if you should use your first dose in a medical setting.
- Use ONZETRA Xsail exactly as your healthcare provider tells you to use it.
- Use a full dose (2 nosepieces) to treat your headache.
- If you do not get any relief after your first full dose, do not use a second dose without first talking with your healthcare provider.
- If your headache comes back after the first full dose or you only get some relief from your headache, you can use a second full dose 2 hours after the first full dose.
- Do not take more than a total of 44 mg (two full doses) of ONZETRA Xsail in a 24-hour period.
- It is not known how using ONZETRA Xsail for a long time affects the nose and throat.
- If you use too much ONZETRA Xsail, call your healthcare provider or go to the nearest hospital emergency room right away.
- You should write down when you have headaches and when you take ONZETRA Xsail so you can talk with your healthcare provider about how ONZETRA Xsail is working for you.

What should I avoid while taking ONZETRA Xsail?

ONZETRA Xsail can cause dizziness, weakness, or drowsiness. If you have these symptoms, do not drive a car, use machinery or do anything where you need to be alert.

What are the possible side effects of ONZETRA Xsail?

ONZETRA Xsail may cause serious side effects. See "What is the most important information I should know about ONZETRA Xsail?"

These serious side effects include:

- changes in color or sensation in your fingers and toes (Raynaud's syndrome)
- stomach and intestinal problems (gastrointestinal and colonic ischemic events). Symptoms of gastrointestinal and colonic ischemic events include:
  - sudden or severe stomach pain
  - stomach pain after meals
  - weight loss
  - nausea or vomiting
  - constipation or diarrhea
  - bloody diarrhea
  - fever
- problems with blood circulation to your legs and feet (peripheral vascular ischemia). Symptoms of peripheral vascular ischemia include:
  - cramping and pain in your legs or hips
  - feeling of heaviness or tightness in your leg muscles
  - burning or aching pain in your feet or toes while resting
  - numbness, tingling or weakness in your legs
  - cold feeling or color changes in 1 or both legs or feet
- hives (itchy bumps); swelling of your tongue, mouth or throat
- medication overuse headaches. Some people who use too much sumatriptan may have worse headaches (medication overuse headache). If your headaches get worse, your healthcare provider may decide to stop your treatment with ONZETRA Xsail.
- serotonin syndrome. Serotonin syndrome is a rare but serious problem that can happen in people using ONZETRA Xsail, especially if ONZETRA Xsail is used with anti-depressant medications called SSRIs or SNRIs. Call your healthcare provider right away if you have any of the following symptoms of serotonin syndrome:
  - Mental changes such as seeing things that are not there (hallucinations), agitation, or coma
  - Fast heartbeat
  - Changes in blood pressure
  - High body temperature
  - Tight muscles
  - Trouble walking
- seizures. Seizures have happened in people taking sumatriptan who have never had seizures before. Talk with your healthcare provider about your chance of having seizures while you take ONZETRA Xsail.

The most common side effects of ONZETRA Xsail include:

- unusual or bad taste in your mouth
- discomfort of your throat or nose
- runny nose, stuffy nose, and/or postnasal drip

Tell your healthcare provider if you have any side effect that bothers you or that does not go away.

These are not all the possible side effects of ONZETRA Xsail. For more information, ask your healthcare provider or pharmacist.

Call your doctor for medical advice about side effects. You may report side effects to FDA at 1-800-FDA-1088.

How should I store ONZETRA Xsail?

- Store at room temperature, between 68°F to 77°F (20°C to 25°C).
- Do not store in the refrigerator or freezer.

Keep ONZETRA Xsail and all medicines out of the reach of children.

General information about the safe and effective use of ONZETRA Xsail.

- ONZETRA Xsail is to be used only with the Xsail breath-powered device.
- Medicines are sometimes prescribed for purposes other than those listed in Patient Information leaflets.
- Do not use ONZETRA Xsail for a condition for which it was not prescribed.
- Do not give ONZETRA Xsail to other people, even if they have the same symptoms you have. It may harm them.

This Patient Information leaflet summarizes the most important information about ONZETRA Xsail. If you would like more information, talk with your healthcare provider. You can ask your healthcare provider or pharmacist for information about ONZETRA Xsail that is written for healthcare professionals.

For more information, go to www.ONZETRA.com or call 1-800-793-2145.

What are the ingredients in ONZETRA Xsail?

- Active ingredient: sumatriptan succinate
- Inactive ingredient: hypromellose (capsule)

This Patient Information has been approved by the U.S. Food and Drug Administration.

Revised: 01/2024

Instructions for Use

Read these Instructions for Use which come with ONZETRA® Xsail® before you start using it and each time you get a refill. Follow these instructions each time you use ONZETRA Xsail.

These Instructions for Use have been approved by the U.S. Food and Drug Administration.

ONZETRA and Xsail are registered trademarks of Currax™ Pharmaceuticals LLC in the United States and other countries. The other brands listed are trademarks of their respective owners and are not trademarks of Currax™ Pharmaceuticals LLC. The makers of these brands are not affiliated with and do not endorse Currax™ Pharmaceuticals LLC or its products.

U.S. Patent Nos, 6,715,485; 7,975,690; 8,047,202; 8,327,844; 8,550,073; 8,555,877; 8,590,530; 8,875,704; 8,899,229; 8,978,647; 9,108,015; 9,119,932

Distributed by:
Currax™ Pharmaceuticals LLC
Brentwood, TN 37027
1-800-793-2145
Issued January 2024

ONZ-LC103.01

© 2024 Currax™ Pharmaceuticals LLC. All rights reserved

PRINCIPAL DISPLAY PANEL - 11 mg Pouch Carton

NDC 42847-311-08

ONZETRA® Xsail®
(sumatriptan nasal powder)
11 mg per nosepiece

Rx Only
For Intranasal Use Only

PLEASE READ INSTRUCTIONS FOR USE.

FOR USE WITH XSAIL®
INTRANASAL DEVICE ONLY

The
Breath Powered®
intranasal medication
delivery system